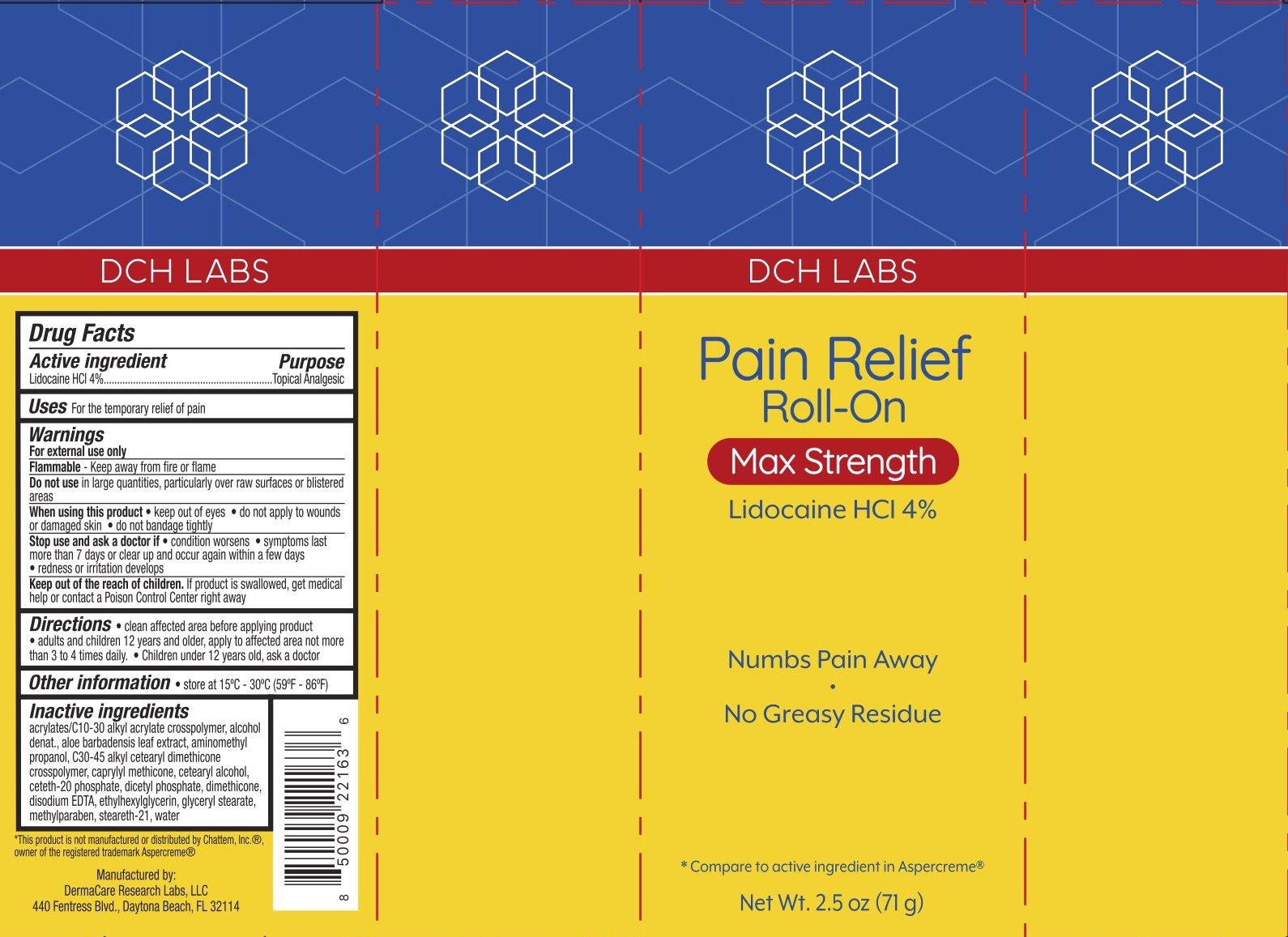 DRUG LABEL: DCH Pain Relief Roll-On
NDC: 72839-087 | Form: GEL
Manufacturer: Derma Care Research Labs, LLC
Category: otc | Type: HUMAN OTC DRUG LABEL
Date: 20241219

ACTIVE INGREDIENTS: LIDOCAINE HYDROCHLORIDE 4 g/100 g
INACTIVE INGREDIENTS: STEARETH-21; ETHYLHEXYLGLYCERIN; GLYCERYL MONOSTEARATE; CETETH-20 PHOSPHATE; CARBOMER COPOLYMER TYPE B (ALLYL PENTAERYTHRITOL CROSSLINKED); ALOE VERA LEAF; AMINOMETHYLPROPANOL; DIHEXADECYL PHOSPHATE; EDETATE DISODIUM; CAPRYLYL TRISILOXANE; METHYLPARABEN; CETOSTEARYL ALCOHOL; WATER; C30-45 ALKYL CETEARYL DIMETHICONE CROSSPOLYMER; DIMETHICONE 200; ALCOHOL

DCH Pain Relief Roll-On

ACTIVE INGREDIENT

Lidocaine HCl 4%

PURPOSE

Topical Analgesic

DOSAGE AND ADMINISTRATION

For the temporary relief of pain and itching.

WARNINGS

For external use only. Flammable--keep away from fire or flame. Do not use in large quantities, particularly over raw surfaces or blistered areas. When using this product keep out of eyes, do not apply to wounds or damaged skin, do not bandage tightly.

Stop use and ask a doctor if the condition worsens, symptoms persist for more than 7 days or clear up and occur again within a few days.

KEEP OUT OF REACH OF CHILDREN

In case of accidental ingestion, seek professional assistance or contact a Poison Control Center immediately.

INDICATIONS AND USAGE

Adults and children 12 years and older: apply to the affected area, not more than 3 to 4 times daily. Children under 12 years of age: ask a doctor.

INACTIVE INGREDIENT

Acrylates/C10-30 Alkyl Acrylate Crosspolymer, Aloe Barbadensis Leaf Extract, Aminomethyl Propanol, C30-45 Alkyl Cetearyl Dimethicone Crosspolymer, Caprylyl Methicone, Cetearyl Alcohol, Ceteth-20 Phosphate, Dicetyl Phosphate, Dimethicone, Disodium EDTA, Ethylhexylglycerin, Glyceryl Stearate, Methylparaben, SD Alcohol 40, Steareth-21, Water.